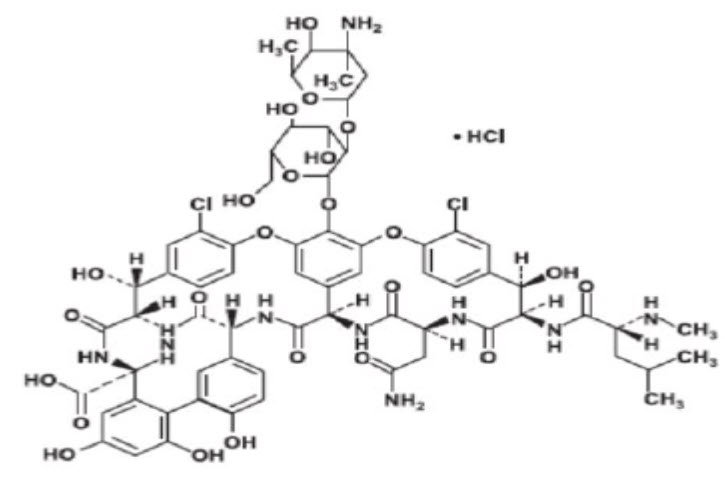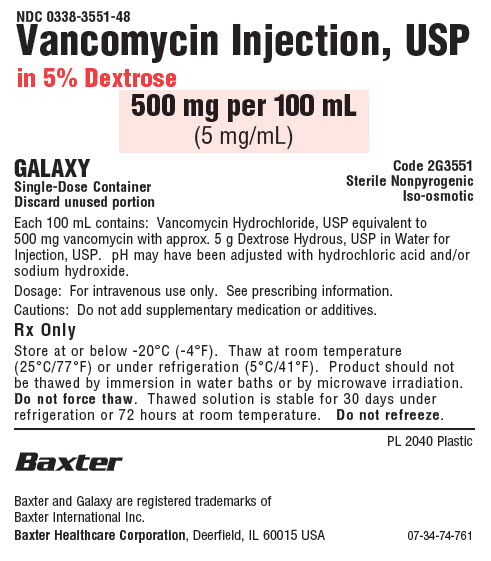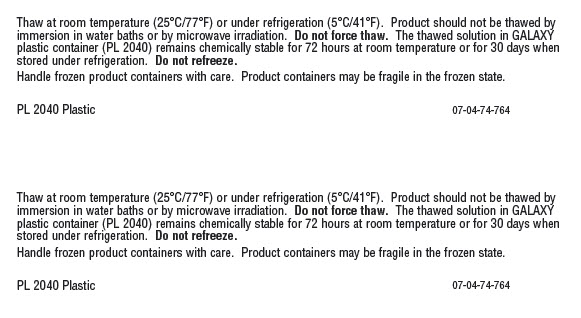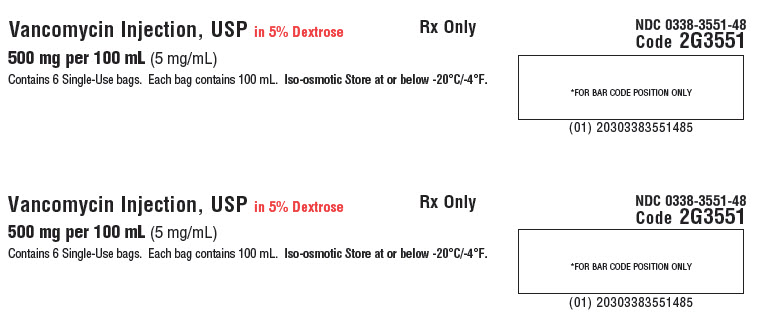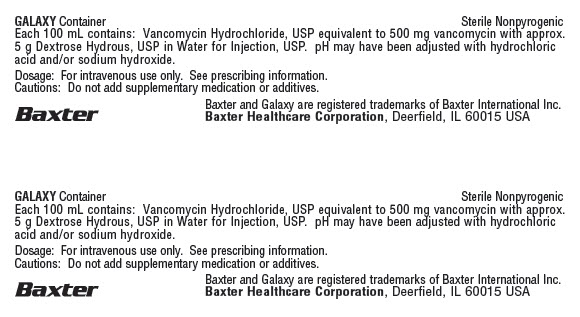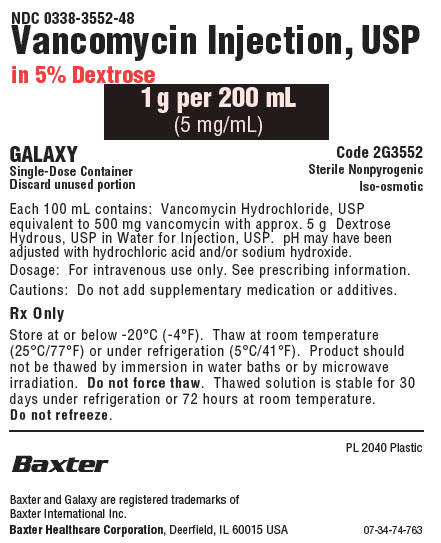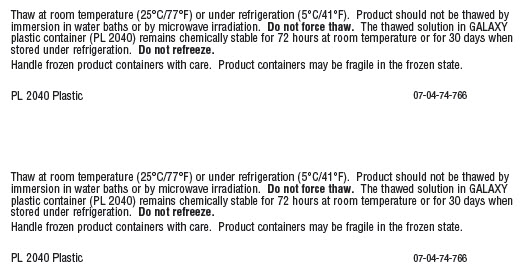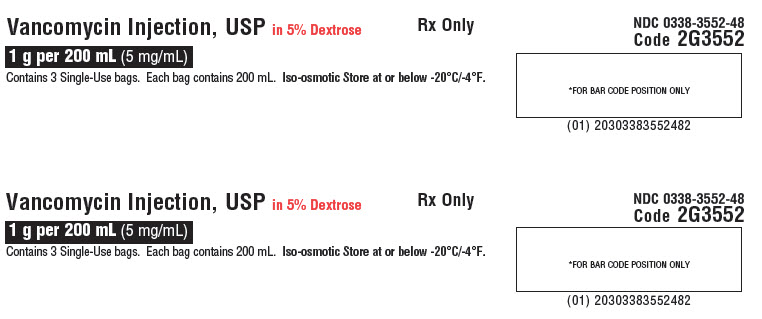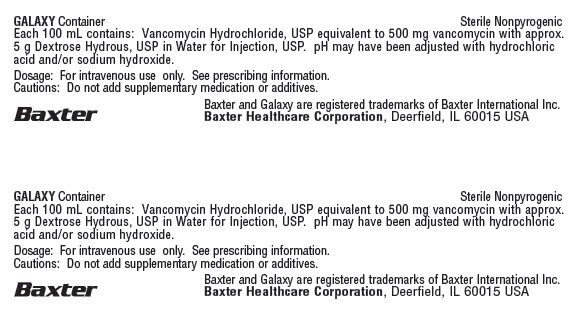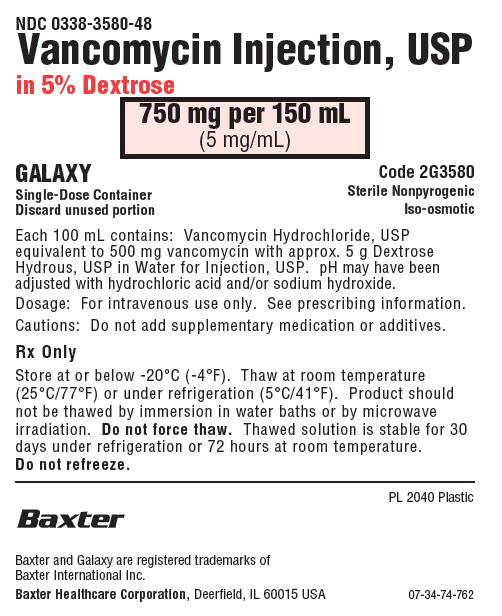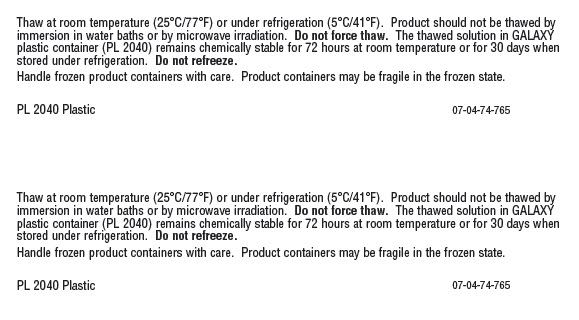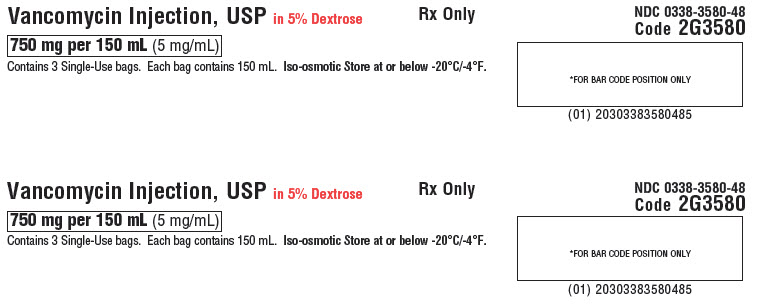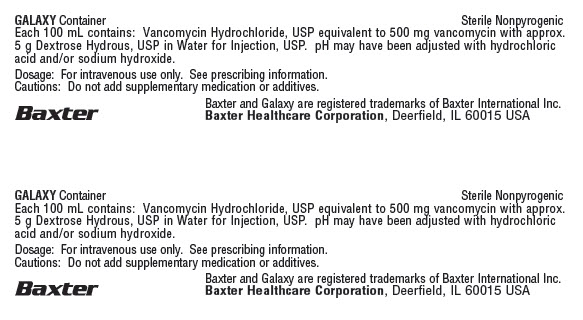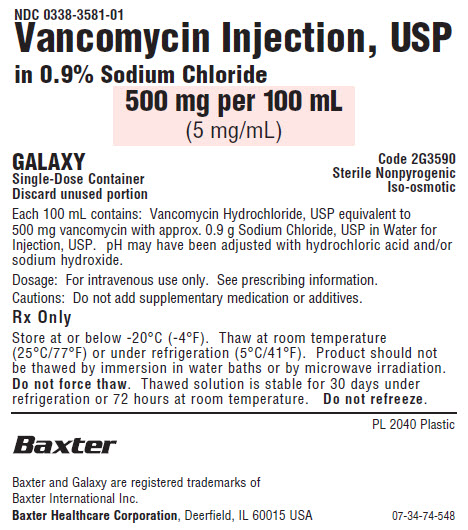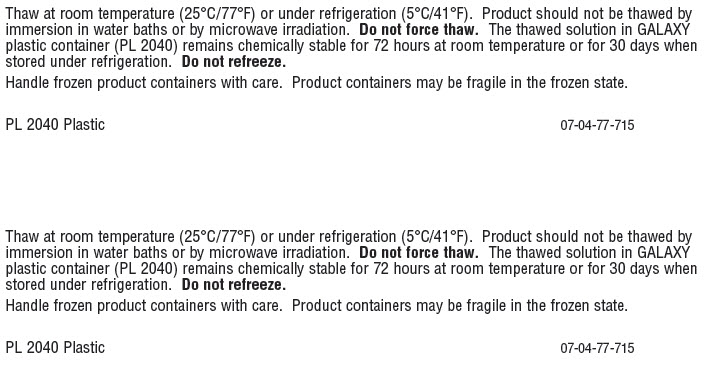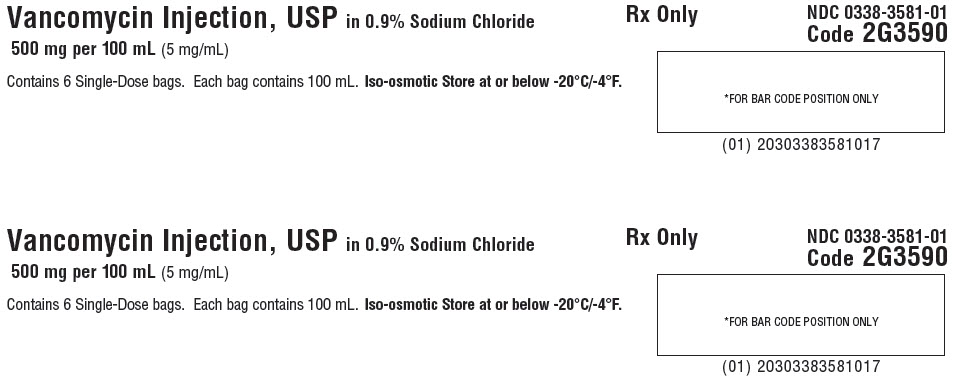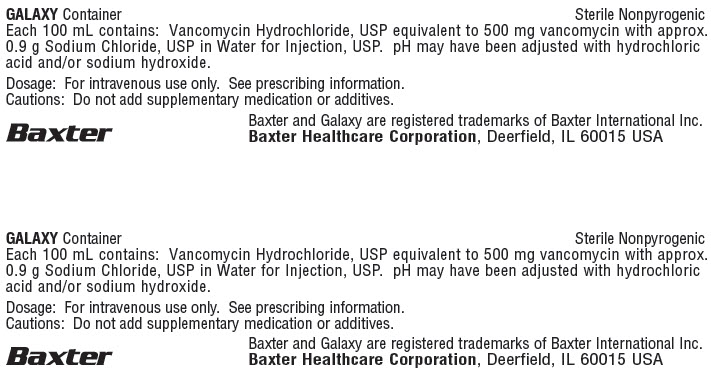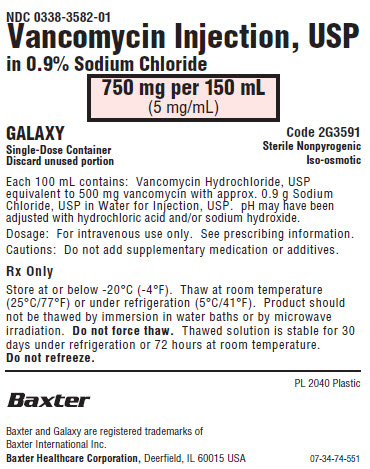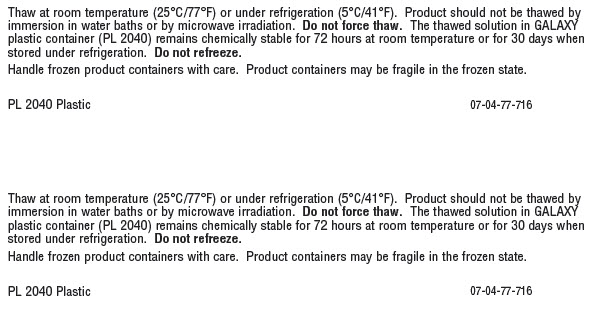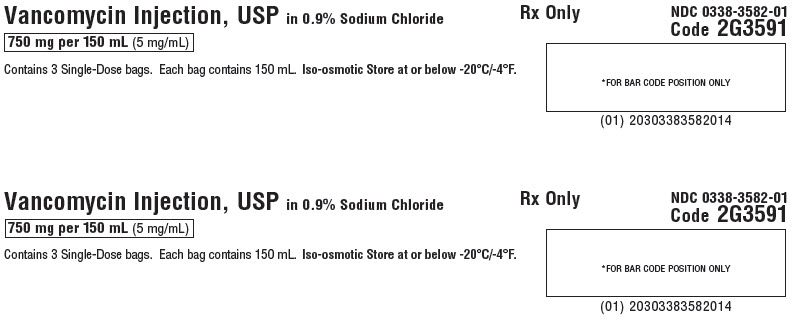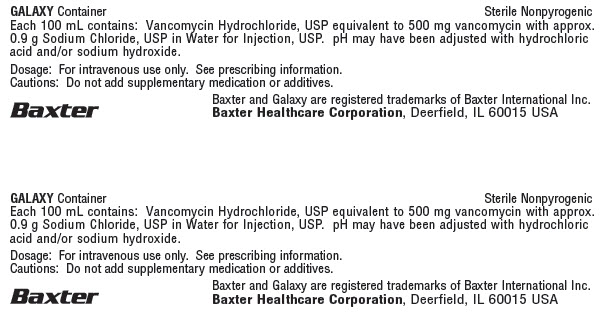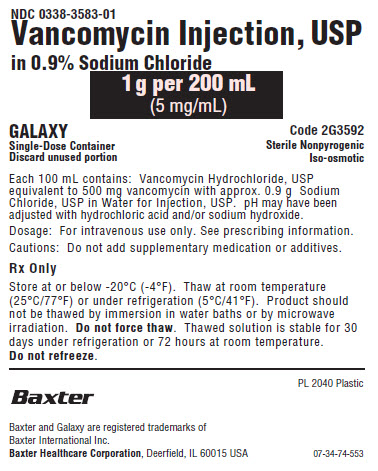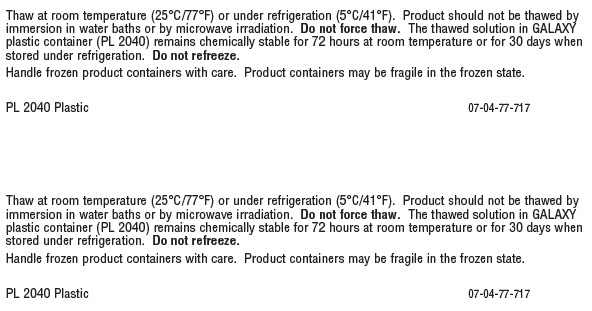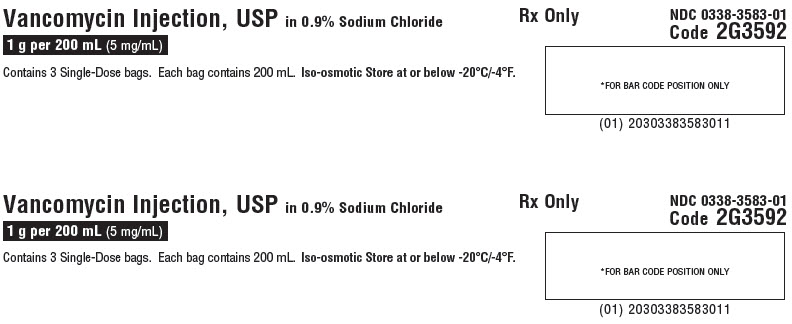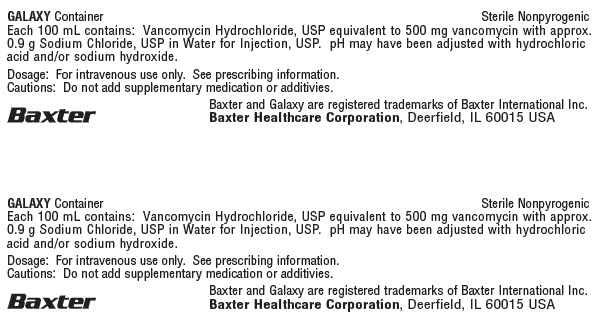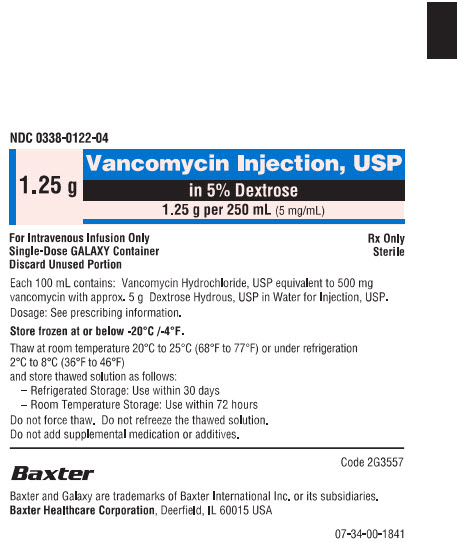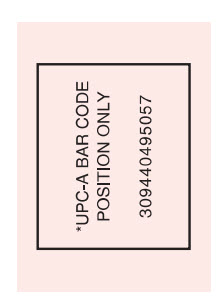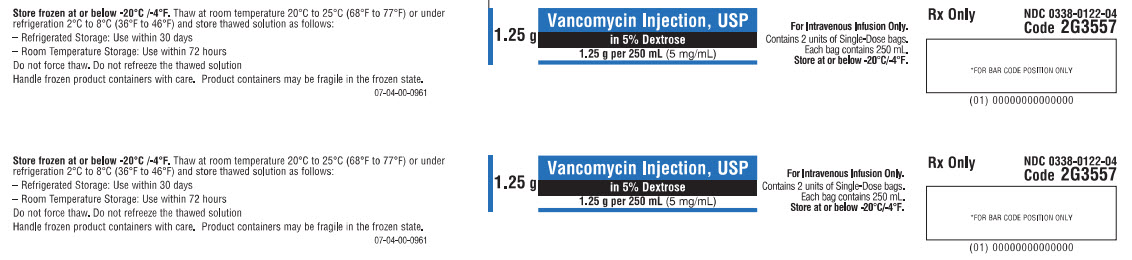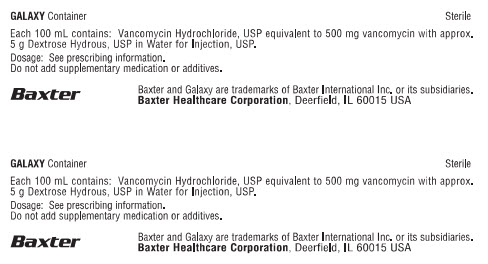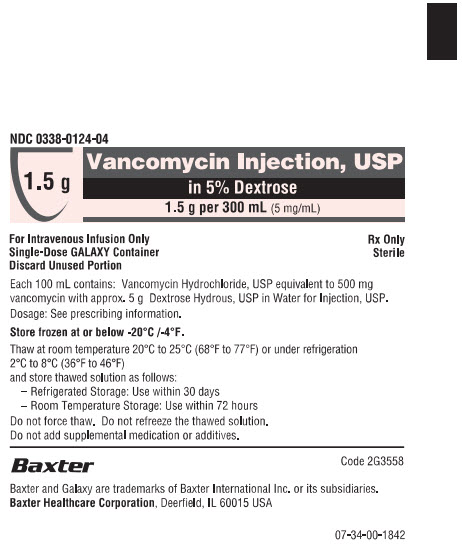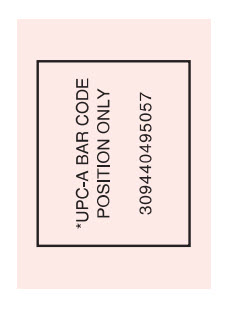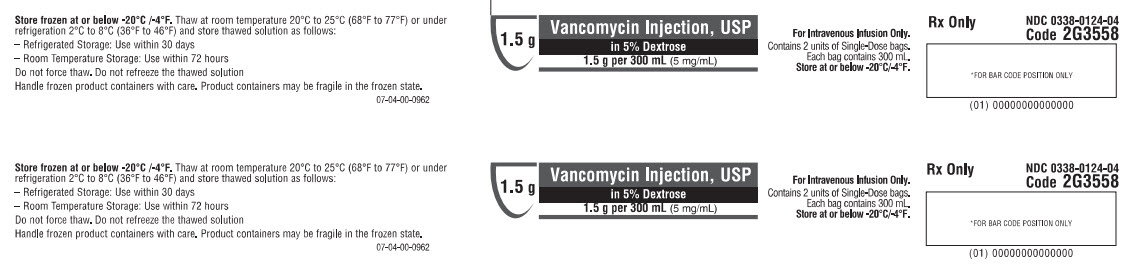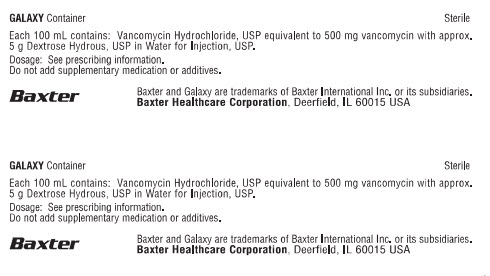 DRUG LABEL: VANCOMYCIN HYDROCHLORIDE
NDC: 0338-3552 | Form: INJECTION, SOLUTION
Manufacturer: Baxter Healthcare Corporation
Category: prescription | Type: HUMAN PRESCRIPTION DRUG LABEL
Date: 20250529

ACTIVE INGREDIENTS: VANCOMYCIN HYDROCHLORIDE 1 g/200 mL
INACTIVE INGREDIENTS: DEXTROSE MONOHYDRATE 10 g/200 mL; WATER; HYDROCHLORIC ACID; SODIUM HYDROXIDE

HIGHLIGHTS OF PRESCRIBING INFORMATION

These highlights do not include all the information needed to use VANCOMYCIN INJECTION safely and effectively. See full prescribing information for VANCOMYCIN INJECTION.
VANCOMYCIN injection, for intravenous use
Initial U.S. Approval: 1958

1 INDICATIONS AND USAGE

Vancomycin Injection is a glycopeptide antibacterial indicated for the treatment of the following infections in adult and pediatric patients for whom appropriate dosing with this formulation can be achieved:

- Septicemia (1.1)
- Infective Endocarditis (1.2)
- Skin and Skin Structure Infections (1.3)
- Bone Infections (1.4)
- Lower Respiratory Tract Infections (1.5)

To reduce the development of drug-resistant bacteria and maintain the effectiveness of Vancomycin Injection and other antibacterial drugs, Vancomycin Injection should be used only to treat or prevent infections that are proven or strongly suspected to be caused by bacteria. (1.6)

2 DOSAGE AND ADMINISTRATION

- If a dose of Vancomycin Injection is required that does not equal 500 mg, 750 mg, 1 g, 1.25 g or 1.5 g, this product is not recommended for use and an alternative formulation of vancomycin should be considered. (2.1)
- For Intravenous use only. Do not administer orally. (2.1).
- Administer Vancomycin Injection by intravenous infusion over 60 minutes or greater to reduce the risk of infusion reactions. (2.1).
- Recommended Dosage in Adult Patients with Normal Renal Function: 2 g divided either as 0.5 grams (g) every 6 hours or 1 g every 12 hours. (2.2)
- Recommended Dosage in Pediatric Patients with Normal Renal Function: 10 mg/kg per dose given every 6 hours. (2.3)
- Recommended Dosage in Patients with Renal Impairment: See full prescribing information for recommended doses in patients with renal impairment. (2.4)
- See full prescribing information for further important preparation and administration instructions. (2.1, 2.5)

3 DOSAGE FORMS AND STRENGTHS

- Injection: Vancomycin Injection (in 5% Dextrose) 500 mg/100 mL; 750 mg/150 mL; 1 g/200 mL; 1.25 g/250 mL; 1.5 g/300 mL (5 mg/mL) in single-dose GALAXY container. (3)
- Injection: Vancomycin Injection (in 0.9% Sodium Chloride) 500 mg/100 mL; 750 mg/150 mL; 1 g/200 mL (5 mg/mL) in single dose GALAXY container. (3)

4 CONTRAINDICATIONS

Hypersensitivity to vancomycin (4)

5 WARNINGS AND PRECAUTIONS

- Infusion Reactions: Hypotension, including shock and cardiac arrest, wheezing, dyspnea, urticaria, muscular and chest pain, and “vancomycin infusion reaction” which manifests as pruritus and erythema that involves the face, neck and upper body may occur with rapid intravenous administration. To reduce the risk of infusion reactions, administer Vancomycin Injection over a period of 60 minutes or greater and also prior to intravenous anesthetic agents. (2.1, 5.1)
- Nephrotoxicity: Monitor renal function in all patients receiving Vancomycin Injection. (5.2)
- Ototoxicity: Serial tests of auditory function may be helpful. (5.3)
- Severe Dermatologic Reactions: Discontinue Vancomycin Injection at the first appearance of signs and symptoms of TEN, SJS, DRESS, AGEP, or LABD. (5.4)
- Clostridioides Difficile-Associated Diarrhea (CDAD): Evaluate patients if diarrhea occurs. (5.5)
- Neutropenia: Periodically monitor leukocyte count. (5.7)
- Phlebitis and Other Administration Site Reactions: Vancomycin is irritating to tissue and must be given by a secure intravenous route of administration. (5.8)
- Risk of High Sodium Load: Avoid use of Vancomycin Injection in patients with congestive heart failure, elderly patients and patients requiring restricted sodium intake. (5.10)

6 ADVERSE REACTIONS

The most common adverse reactions are anaphylaxis, “vancomycin infusion reaction”, acute kidney injury, hearing loss, neutropenia. (6)

To report SUSPECTED ADVERSE REACTIONS, contact Baxter Healthcare at 1-866-888-2472 or FDA at 1-800-FDA-1088 or www.fda.gov/medwatch.

7 DRUG INTERACTIONS

- Anesthetic Agents: Concomitant administration of vancomycin and anesthetic agents has been associated with erythema and histamine-like flushing. (2.1, 7.1)
- Piperacillin/Tazobactam: Increased incidence of acute kidney injury in patients receiving concomitant piperacillin/tazobactam and vancomycin as compared to vancomycin alone. Monitor kidney function in patients. (7.2)

FULL PRESCRIBING INFORMATION

1 INDICATIONS AND USAGE

1.1 Septicemia

Vancomycin Injection is indicated in adults and pediatric patients for whom appropriate dosing with this formulation can be achieved [see Dosage and Administration (2) and Use in Specific Populations (8.4)] for the treatment of septicemia due to:

- Susceptible isolates of methicillin-resistant Staphylococcus aureus (MRSA) and coagulase negative staphylococci.
- Methicillin-susceptible staphylococci in penicillin-allergic patients, or those patients who cannot receive or who have failed to respond to other drugs, including penicillins or cephalosporins.

1.2 Infective Endocarditis

Vancomycin Injection is indicated in adults and pediatric patients for whom appropriate dosing with this formulation can be achieved [see Dosage and Administration (2) and Use in Specific Populations (8.4)] for the treatment of infective endocarditis due to:

- Susceptible isolates of MRSA.
- Viridans group streptococci or Streptococcus gallolyticus (previously known as Streptococcus bovis) and Enterococcus species and Corynebacterium species. For enterococcal endocarditis (e.g., E. faecalis), use Vancomycin Injection in combination with an aminoglycoside.
- Methicillin-susceptible staphylococci in penicillin-allergic patients, or those patients who cannot receive or who have failed to respond to other drugs, including penicillins or cephalosporins.

Vancomycin Injection is indicated in adults and pediatric patients for the treatment of early-onset prosthetic valve endocarditis caused by Staphylococcus epidermidis in combination with rifampin and an aminoglycoside.

1.3 Skin and Skin Structure Infections

Vancomycin Injection is indicated in adults and pediatric patients for whom appropriate dosing with this formulation can be achieved [see Dosage and Administration (2) and Use in Specific Populations (8.4)] for the treatment of skin and skin structure infections due to:

- Susceptible isolates of MRSA and coagulase negative staphylococci.
- Methicillin-susceptible staphylococci in penicillin-allergic patients, or those patients who cannot receive or who have failed to respond to other drugs, including penicillins or cephalosporins.

1.4 Bone Infection

Vancomycin Injection is indicated in adults and pediatric patients (and older) for whom appropriate dosing with this formulation can be achieved [see Dosage and Administration (2) and Use in Specific Populations (8.4)] for the treatment of bone infections due to:

- Susceptible isolates of MRSA and coagulase negative staphylococci.
- Methicillin-susceptible staphylococci in penicillin-allergic patients, or those patients who cannot receive or who have failed to respond to other drugs, including penicillins or cephalosporins.

1.5 Lower Respiratory Tract Infections

Vancomycin Injection is indicated in adults and pediatric patients for whom appropriate dosing with this formulation can be achieved [see Dosage and Administration (2) and Use in Specific Populations (8.4)] for the treatment of lower respiratory tract infections due to:

- Susceptible isolates of MSRA.
- Methicillin-susceptible staphylococci in penicillin-allergic patients, or those patients who cannot receive or who have failed to respond to other drugs, including penicillins or cephalosporins.

1.6 Usage

To reduce the development of drug-resistant bacteria and maintain the effectiveness of Vancomycin Injection and other antibacterial drugs, Vancomycin Injection should be used only to treat or prevent infections that are proven or strongly suspected to be caused by susceptible bacteria. When culture and susceptibility information are available, they should be considered in selecting or modifying antibacterial therapy. In the absence of such data, local epidemiology and susceptibility patterns may contribute to the empiric selection of therapy.

2 DOSAGE AND ADMINISTRATION

2.1 Important Administration Instructions

- If a dose of Vancomycin Injection is required that does not equal 500 mg, 750 mg, 1 g, 1.25 g or 1.5 g, this product is not recommended for use and an alternative formulation of vancomycin should be considered.
- Vancomycin Injection is intended for intravenous use only.
- Vancomycin Injection is not to be administered orally.
- To reduce the risk of infusion related adverse reactions, administer Vancomycin Injection by intravenous infusion over 60 minutes or greater [see Warnings and Precautions (5.1) and Adverse Reactions (6.1)]. An infusion rate of 10 mg/min or less is associated with fewer infusion-related adverse reactions [see Warnings and Precautions (5.1) and Adverse Reactions (6.1)]. Infusion related adverse reactions may occur, however, at any rate or concentration.
- Drug additives should not be made to this solution.
- Vancomycin Injection concentrations of no more than 5 mg/mL are recommended in adults [see Dosage and Administration (2.2)]. See also age-specific recommendations [see Dosage and Administration (2.3)].
- Administer Vancomycin by a secure intravenous route of administration to reduce the risk of local irritation and phlebitis reactions [see Warnings and Precautions (5.8)].
- Administer Vancomycin Injection prior to intravenous anesthetic agents to reduce the risk of infusion related adverse reactions [see Warnings and Precautions (5.1)].

2.2 Recommended Dosage in Adult Patients with Normal Renal Function

The usual daily intravenous dosage of Vancomycin Injection is 2 grams (g) divided either as 500 mg every 6 hours or 1 g every 12 hours. Administer each dose by intravenous infusion over a period of 60 minutes or greater. Other patient factors, such as age or obesity, may call for modification of the usual intravenous daily dose. The initial daily dose should be no less than 15 mg/kg.

2.3 Recommended Dosage in Pediatric Patients with Normal Renal Function

If a dose of Vancomycin Injection is required that does not equal 500 mg, 750 mg, 1 g, 1.25 g or 1.5 g, this product is not recommended for use and an alternative formulation of vancomycin should be considered [see Use in Specific Populations (8.4)].

Pediatric Patients (Aged 1 Month and Older)

The usual intravenous dosage of vancomycin is 10 mg/kg per dose given every 6 hours. Each dose should be administered over a period of at least 60 minutes. Close monitoring of serum concentrations of vancomycin may be warranted in these patients.

Pediatric Patients (Younger than 1 Month Old)

In pediatric patients up to the age of 1 month, the total daily intravenous dosage may be lower. In neonates, an initial dose of 15 mg/kg is suggested, followed by 10 mg/kg every 12 hours for neonates in the 1st week of life and every 8 hours thereafter up to the age of 1 month. Each dose should be administered over 60 minutes. In premature infants, vancomycin clearance decreases as postconceptional age decreases. Therefore, longer dosing intervals may be necessary in premature infants. Close monitoring of serum concentrations of vancomycin is recommended in these patients.

2.4 Recommended Dosage in Patients with Renal Impairment

Dosage adjustment must be made in patients with renal impairment. The initial dose should be no less than 15 mg/kg in patients with any degree of renal impairment. Measure trough vancomycin serum concentrations to guide therapy, especially in seriously ill patients with changing renal function.

For functionally anephric patients, an initial dose of 15 mg/kg of body weight should be given to achieve prompt therapeutic serum concentrations. Measure vancomycin serum concentrations at 24 hours following the first dose to guide further intravenous therapy.

2.5 Administration and Preparation Instructions for Vancomycin Injection

Administration Instructions

Vancomycin Injection, in GALAXY plastic container is for intravenous administration only. Intermittent infusion is the recommended method of administration.

Store the frozen Vancomycin Injection container in a freezer capable of maintaining a temperature at or below -20°C (-4°F) [see How Supplied/Storage and Handling (16)].

Preparation for Intravenous Administration:

Thawing of Plastic Containers

1. Thaw frozen containers at room temperature (25°C/77°F) or under refrigeration (5°C/41°F). Product should not be thawed by immersion in waters baths or by microwave irradiation. Do not force thaw.
2. Check for minute leaks by squeezing the bag firmly. If leaks are detected, discard solution because sterility may be impaired.
3. Do not add supplemental medication.
4. Visually inspect the container. If the outlet port protector is damaged, detached, or not present, discard container as solution path sterility may be impaired.
5. Components of the solution may precipitate in the frozen state and will dissolve upon reaching room temperature with little or no agitation. Potency is not affected. Agitate after solution has reached room temperature.
6. If after visual inspection the solution remains cloudy or if an insoluble precipitate is noted or if any seals are not intact, discard the container.
7. The thawed solution in GALAXY plastic container remains chemically stable for 72 hours at room temperature (25°C/77°F) or for 30 days when stored under refrigeration (5°C/41°F).
8. Handle frozen product containers with care. Product containers may be fragile in the frozen state.
9. Do not refreeze thawed Vancomycin Injection.
Directions for Administration

Parenteral drug products should be inspected visually for particulate matter and discoloration prior to administration.

1. Suspend container from eyelet support.
2. Remove protector from outlet port at bottom of container.
3. Attach administration set. Refer to complete directions accompanying set.
4. Use sterile equipment.

Do not use plastic containers in series connections. Such use could result in an embolism due to residual air being drawn from the primary container before administration of the fluid from the secondary container is complete.

3 DOSAGE FORMS AND STRENGTHS

Injection: Vancomycin Injection USP, is a frozen, iso-osmotic, sterile, nonpyrogenic premixed solution available in the following strengths:

- 500 mg/100 mL (5 mg/mL); Each 100 mL single-dose GALAXY container contains 500 mg Vancomycin (as Vancomycin hydrochloride) in 5% Dextrose or 0.9% Sodium Chloride.
- 750 mg/150 mL (5 mg/mL); Each 150 mL single-dose GALAXY container contains 750 mg Vancomycin (as Vancomycin hydrochloride) in 5% Dextrose or 0.9% Sodium Chloride.
- 1 g/200 mL (5 mg/mL); Each 200 mL single-dose GALAXY container contains 1 g Vancomycin (as Vancomycin hydrochloride) in 5% Dextrose or 0.9% Sodium Chloride.
- 1.25 g/250 mL (5 mg/mL): Each 250 mL single-dose GALAXY container contains 1.25 g of Vancomycin (as Vancomycin hydrochloride) in 5 % Dextrose.
- 1.5 g/300 mL (5 mg/mL): Each 250 mL single-dose GALAXY container contains 1.5 g of Vancomycin (as Vancomycin hydrochloride) in 5 % Dextrose.

4 CONTRAINDICATIONS

- Vancomycin Injection is contraindicated in patients with known hypersensitivity to vancomycin.
- Solutions containing dextrose including Vancomycin Injection, may be contraindicated in patients with a known allergy to corn or corn products.

5 WARNINGS AND PRECAUTIONS

5.1 Infusion Reactions

Hypotension including shock and cardiac arrest, wheezing, dyspnea, urticaria or pruritus, muscular and chest pain may occur with rapid Vancomycin Injection administration. (e.g., over several minutes). The reactions may be more severe in pediatric patients [see Use in Specific Populations (8.4)].

Rapid intravenous administration of Vancomycin Injection may also be associated with “vancomycin infusion reaction”, which manifests as pruritus and erythema that involves the face, neck and upper body or pain and muscle spasm of the chest and back. There have been reports that the frequency of infusion-related reactions (including hypotension, flushing, erythema, urticaria, and pruritus) increases with the concomitant administration of anesthetic agents.

Infusion-related adverse reactions are related to both the concentration and the rate of administration of Vancomycin for Injection. Infusion-related adverse reactions may occur, however, at any rate or concentration.

Administer Vancomycin Injection over a period of 60 minutes or greater to reduce the risk of rapid-infusion-related adverse reactions. In selected patients in need of fluid restriction, a concentration up to 10 mg/mL may be used; use of such higher concentrations may increase the risk of infusion-related adverse reactions.

Administer Vancomycin Injection as a 60-minute infusion prior to administration of anesthetic agents when feasible to minimize infusion-related adverse reactions. Stop the infusion if a reaction occurs because this usually results in prompt cessation of these reactions.

5.2 Nephrotoxicity

Vancomycin Injection can result in acute kidney injury (AKI), including acute renal failure, mainly due to interstitial nephritis or less commonly acute tubular necrosis. AKI is manifested by increasing blood urea nitrogen (BUN) and serum creatinine (Cr). The risk of AKI increases with higher vancomycin serum levels, prolonged exposure, concomitant administration of other nephrotoxic drugs, concomitant administration of piperacillin-tazobactam [see Drug Interactions (7.2)], volume depletion, pre-existing renal impairment and in critically ill patients and patients with co-morbid conditions that predispose to renal impairment.

Monitor serum vancomycin concentrations and renal function in all patients receiving Vancomycin Injection. More frequent monitoring is recommended in patients with comorbidities that predispose to impairment in renal function or are concomitantly receiving other nephrotoxic drugs, in critically ill patients, in patients with changing renal function, and in patients requiring higher therapeutic vancomycin levels. If acute kidney injury occurs, discontinue Vancomycin Injection, or reduce the dose [see Dosage and Administration (2.4)].

5.3 Ototoxicity

Ototoxicity has occurred in patients receiving Vancomycin Injection. It may be reversible or permanent. Ototoxicity manifests as tinnitus, hearing loss, dizziness or vertigo. The risk is higher in older patients, patients who are receiving higher doses, who have an underlying hearing loss, who are receiving concomitant therapy with another ototoxic agent, such as an aminoglycoside or who have underlying renal impairment. Monitor for signs and symptoms of ototoxicity during therapy. Monitor serum vancomycin concentrations and renal function in all patients receiving parenteral vancomycin. Discontinue Vancomycin Injection if ototoxicity occurs. Dosage of Vancomycin Injection must be adjusted for patients with renal impairment [see Dosage and Administration (2.4)].

Serial tests of auditory function may be helpful in order to minimize the risk of ototoxicity.

5.4 Severe Dermatologic Reactions

Severe dermatologic reactions such as toxic epidermal necrolysis (TEN), Stevens-Johnson syndrome (SJS), drug reaction with eosinophilia and systemic symptoms (DRESS), acute generalized exanthematous pustulosis (AGEP), and linear IgA bullous dermatosis (LABD) have been reported in association with the use of vancomycin. Cutaneous signs or symptoms reported include skin rashes (including exfoliative dermatitis), mucosal lesions, and blisters.

Discontinue Vancomycin Injection at the first appearance of signs and symptoms of TEN, SJS, DRESS, AGEP, or LABD.

5.5 Clostridioides Difficile-Associated Diarrhea (CDAD)

Clostridioides difficile-associated diarrhea (CDAD) has been reported with use of nearly all antibacterial agents, including Vancomycin Injection, and may range in severity from mild diarrhea to fatal colitis. Treatment with antibacterial agents alters the normal flora of the colon leading to overgrowth of C. difficile.

C. difficile produces toxins A and B which contribute to the development of CDAD. Hypertoxin producing strains of C. difficile cause increased morbidity and mortality, as these infections can be refractory to antimicrobial therapy and may require colectomy. CDAD must be considered in all patients who present with diarrhea following antibacterial use. Careful medical history is necessary since CDAD has been reported to occur over two months after the administration of antibacterial agents.

If CDAD is suspected or confirmed, ongoing antibacterial use not directed against C. difficile may need to be discontinued. Appropriate fluid and electrolyte management, protein supplementation, antibacterial treatment of C. difficile, and surgical evaluation should be instituted as clinically indicated.

Prolonged use of vancomycin may result in the overgrowth of nonsusceptible microorganisms. Careful observation of the patient is essential. If superinfection occurs during therapy, appropriate measures should be taken. In rare instances, there have been reports of pseudomembranous colitis due to C. difficile developing in patients who received intravenous vancomycin.

5.6 Hemorrhagic Occlusive Retinal Vasculitis (HORV)

Hemorrhagic occlusive retinal vasculitis, including permanent loss of vision, occurred in patients receiving intracameral or intravitreal administration of vancomycin during or after cataract surgery. The safety and efficacy of vancomycin administered by the intracameral or the intravitreal route have not been established by adequate and well-controlled trials. Vancomycin is not indicated for prophylaxis of endophthalmitis.

5.7 Neutropenia

Reversible neutropenia has been reported in patients receiving vancomycin [see Adverse Reactions (6.1)]. Patients who will undergo prolonged therapy with vancomycin or those who are receiving concomitant drugs that may cause neutropenia should have periodic monitoring of the leukocyte count.

Reversible neutropenia, usually starting 1 week or more after onset of therapy with vancomycin or after a total dosage of more than 25 g, has been reported for several dozen patients. Neutropenia appears to be promptly reversible when vancomycin is discontinued. Thrombocytopenia has been reported. Although a causal relationship has not been established, reversible agranulocytosis (granulocytes <500/mm^3) has been reported.

5.8 Phlebitis and Other Administration Site Reactions

Inflammation at the injection site has been reported. Vancomycin is irritating to tissue and must be given by a secure intravenous route of administration. Thrombophlebitis may occur, the frequency and severity of which can be minimized by slow infusion of the drug and by rotation of venous access sites.

Administration of Vancomycin Injection by intramuscular (IM), intraperitoneal, intrathecal intraventricular, or intravitreal routes has not been approved and is not recommended. The safety and efficacy of vancomycin administered by these routes of administration have not been established by adequate and well controlled trials. Pain, tenderness, and necrosis occur with intramuscular (IM) injection of vancomycin or with inadvertent extravasation. There have been reports that the frequency of infusion-related events (including hypotension, flushing, erythema, urticaria, and pruritus) increases with the concomitant administration of anesthetic agents. Infusion-related events may be minimized by the administration of vancomycin as a 60-minute infusion prior to anesthetic induction.

Administration of sterile vancomycin by the intraperitoneal route during continuous ambulatory peritoneal dialysis (CAPD) has been reported to result in a syndrome of chemical peritonitis. Manifestations of this syndrome range from a cloudy dialysate alone to a cloudy dialysate accompanied by variable degrees of abdominal pain and fever. This syndrome appears to be resolved after discontinuation of intraperitoneal vancomycin.

About 60% of an intraperitoneal dose of vancomycin administered during peritoneal dialysis is absorbed systemically in 6 hours. Serum concentrations of about 10 mcg/mL are achieved by intraperitoneal injection of 30 mg/kg of vancomycin. However, the safety and efficacy of the intraperitoneal use of vancomycin has not been established in adequate and well-controlled trials.

5.9 Development of Drug-Resistant Bacteria

Prescribing Vancomycin Injection in the absence of a proven or strongly suspected bacterial infection or a prophylactic indication is unlikely to provide benefit to the patient and increases the risk of the development of drug-resistant bacteria.

5.10 Risk of High Sodium Load

Each 100 mL solution of Vancomycin Injection contains 354 mg of sodium, each 150 mL solution of Vancomycin Injection contains 531 mg of sodium, and each 200 mL solution of Vancomycin Injection contains 708 mg of sodium. Avoid use of Vancomycin Injection, in patients with congestive heart failure, elderly patients and patients requiring restricted sodium intake.

6 ADVERSE REACTIONS

The following clinically significant adverse reactions are described elsewhere in the labeling:

- Infusion Reactions [see Warnings and Precautions (5.1)]
- Nephrotoxicity [see Warnings and Precautions (5.2)]
- Ototoxicity [see Warnings and Precautions (5.3)]
- Severe Dermatologic Reactions [see Warnings and Precautions (5.4)]
- Clostridioides Difficile-Associated Diarrhea [see Warnings and Precautions (5.5)]
- Hemorrhagic Occlusive Retinal Vasculitis [see Warnings and Precautions (5.6)]
- Neutropenia [see Warnings and Precautions (5.7)]
- Phlebitis and Other Administration Site Reactions [see Warnings and Precautions (5.8)].

6.1 Clinical Trials Experience

Because clinical trials are conducted under widely varying conditions, adverse reaction rates observed in the clinical trials of a drug cannot be directly compared to rates in the clinical trials of another drug and may not reflect the rates observed in practice. The following adverse reactions associated with the use of vancomycin were identified in clinical trials:

Immune System Disorders: Anaphylaxis and “vancomycin infusion reaction”

Renal and urinary Disorders: Acute kidney injury and interstitial nephritis

Ear and Labyrinth Disorders: Hearing loss, vertigo, and tinnitus

Skin and subcutaneous tissue disorders: Rashes including exfoliative dermatitis, and Stevens-Johnson syndrome (SJS)

Gastrointestinal Disorders: Clostridioides difficile colitis, nausea

Blood and Lymphatic System Disorders: Agranulocytosis, neutropenia, pancytopenia, leukopenia, thrombocytopenia, eosinophilia

Cardiac Disorders: Cardiac arrest, chest pain

General Disorders and Administration Site Conditions: General discomfort, drug fever, chills, phlebitis, injection site irritation, injection site pain and necrosis following intramuscular injection, chemical peritonitis following intraperitoneal administration (Vancomycin Injection is not approved for intramuscular and intraperitoneal administration)

Laboratory Abnormalities: Elevated blood urea nitrogen, elevated serum creatinine

Musculoskeletal and connective tissue disorders: Muscle pain

Nervous system disorders: Dizziness

Respiratory, thoracic and mediastinal disorders: Wheezing, dyspnea

Vascular disorders: Hypotension, shock, vasculitis

6.2 Postmarketing Experience

The following adverse reactions have been identified during postmarketing use of vancomycin. Because these reactions are reported voluntarily from a population of uncertain size, it is not possible to reliably estimate their frequency or establish a causal relationship to drug exposure.

Immune System Disorders:Acute myocardial ischemia with or without myocardial infarction may occur as part of an allergic reaction.

Skin and Subcutaneous Tissue Disorders: Severe dermatologic reactions such as toxic epidermal necrolysis (TEN), Drug reaction with eosinophilia and systemic symptoms (DRESS), acute generalized exanthematous pustulosis (AGEP), and linear IgA bullous dermatosis (LABD).

7 DRUG INTERACTIONS

7.1 Anesthetic Agents

Concomitant administration of vancomycin and anesthetic agents has been associated with erythema and histamine-like flushing [see Warnings and Precautions (5.1) and Use in Specific Populations (8.4)].

7.2 Piperacillin-Tazobactam

Studies have detected an increased incidence of acute kidney injury in patients administered concomitant piperacillin/tazobactam and vancomycin as compared to vancomycin alone. Monitor kidney function in patients receiving concomitant piperacillin/tazobactam and Vancomycin Injection. No pharmacokinetic interactions have been noted between piperacillin/tazobactam and vancomycin.

7.3 Ototoxic and/or Nephrotoxic Drugs

Concurrent and/or sequential systemic or topical use of other potentially neurotoxic and/or nephrotoxic drugs with Vancomycin Injection requires more frequent monitoring of renal function.

8 USE IN SPECIFIC POPULATIONS

8.1 Pregnancy

Risk Summary

Available data over several decades of vancomycin use in pregnant women have not identified a drug-associated risk of major birth defects, miscarriage, or adverse maternal or fetal outcomes (see Data). Vancomycin did not show adverse developmental effects when administered intravenously to pregnant rats and rabbits during organogenesis at doses less than or equal to the recommended maximum human dose (see Data).

The background risk of major birth defects and miscarriage for the indicated population is unknown. All pregnancies have a background risk of birth defect, loss, or other adverse outcomes. In the U.S. general population, the estimated background risk of major birth defects and miscarriage in clinically recognized pregnancies is 2% to 4% and 15% to 20%, respectively.

Data

Human Data

A published study evaluated hearing loss and nephrotoxicity in infants of 10 pregnant intravenous drug users treated with intravenously administered vancomycin for suspected or documented methicillin-resistant Staphylococcus-aureus (MRSA) in the second or third trimester. The comparison groups were 10 non-intravenous drug-dependent patients who received no treatment, and 10 untreated intravenous drug-dependent patients who served as substance abuse controls. No infant in the vancomycin exposed group had abnormal sensorineural hearing at 3 months of age or nephrotoxicity.

A published prospective study assessed outcomes in 55 pregnant women with a positive Group B streptococcus (GBS) culture and a high-risk penicillin allergy with resistance to clindamycin or unknown sensitivity who were administered vancomycin at the time of delivery. Vancomycin dosing ranged from the standard 1 g intravenously every 12 hours to 20 mg/kg intravenous every 8 hours (maximum individual dose 2 g). No major adverse reactions were recorded either in the mothers or their newborns.

None of the newborns had sensorineural hearing loss. Neonatal renal function was not examined, but all of the newborns were discharged in good condition.

Animal Data

Vancomycin did not cause fetal malformations when administered during organogenesis to pregnant rats (gestation days 6 to 15) and rabbits (gestation days 6 to 18) at the equivalent recommended maximum human dose (based on body surface area comparisons) of 200 mg/kg/day IV to rats or 120 mg/kg/day IV to rabbits. No effects on fetal weight or development were seen in rats at the highest dose tested or in rabbits given 80 mg/kg/day (approximately 1 and 0.8 times the recommended maximum human dose based on body surface area, respectively). Maternal toxicity was observed in rats (at doses 120 mg/kg and above) and rabbits (at 80 mg/kg and above).^1

8.2 Lactation

Risk Summary

Vancomycin is present in human milk following intravenous administration, however, there are insufficient data to inform the levels. There are no data on the effects of vancomycin on the breastfed infant or milk production. The developmental and health benefits of breastfeeding should be considered along with the mother’s clinical need for vancomycin and any potential adverse effects on the breastfed infant from vancomycin or from the underlying maternal condition.

8.4 Pediatric Use

Vancomycin Injection is indicated in pediatric patients for the treatment of septicemia, infective endocarditis, skin and skin structure infections, bone infections and lower respiratory tract infections for whom appropriate dosing with this formulation can be achieved [see Indications and Usage (1.1 to 1.5) and Dosage and Administration (2.1, 2.3)].

Because of the limitations of the available strengths and administration requirements (i.e., administration of fractional doses is not recommended) of Vancomycin Injection, and to avoid unintentional overdose, this product is not recommended for use if a dose of Vancomycin Injection that does not equal 500 mg, 750 mg, 1 g, 1.25 g or 1.5 g is required, and an alternative formulation of vancomycin should be considered [see Dosage and Administration (2.1, 2.3)].

More severe infusion related reactions related to vancomycin administration may occur in pediatric patients. In pediatric patients, monitor vancomycin serum concentration and renal function when administering Vancomycin injection [see Dosage and Administration (2.3) and Warnings and Precautions (5.2)]. Concomitant administration of vancomycin and intravenous anesthetic agents has been associated with erythema and histamine-like flushing in all patients including pediatric patients [see Warnings and Precautions (5.1)].

8.5 Geriatric Use

Vancomycin injection is known to be substantially excreted by the kidney, and the risk of adverse reactions to this drug may be greater in patients with impaired renal function. Because elderly patients are more likely to have decreased renal function, care should be taken in dose selection [see Dosage and Administration (2.4)], and it may be useful to monitor renal function [see Warnings and Precautions (5.2)].

8.6 Renal Impairment

Dosage adjustment of Vancomycin Injection must be made in patients with impaired renal function [see Dosage and Administration (2.4)]. Measure trough vancomycin serum concentrations to guide intravenous therapy, especially in patients with impaired renal function or fluctuating renal function.

10 OVERDOSAGE

Supportive care is advised, with maintenance of glomerular filtration. Vancomycin is poorly removed by dialysis.

Hemofiltration and hemoperfusion with polysulfone resin have been reported to result in increased vancomycin clearance.

For current information on the management of overdosage, contact the National Poison Control Center at 1-800-222-1222 or www.poison.org.

11 DESCRIPTION

Vancomycin Injection USP, in the GALAXY plastic container contains vancomycin, added as Vancomycin Hydrochloride USP. It is a tricyclic glycopeptide antibacterial derived from Amycolatopsis orientalis (formerly Nocardia orientalis). The chemical name of vancomycin hydrochloride is (Sa)-(3S, 6R, 7R, 22R, 23S, 26S, 36R, 38aR)-44-[[2-O-(3-Amino-2, 3, 6-trideoxy-3-Cmethyl-α-L-lyxo-hexopyranosyl)-β-D-glucopyranosyl]oxy]-3-(carbamoylmethyl)- 10,19dichloro 2,3,4,5,6,7,23,24,25,26,36,37,38,38a-tetradecahydro-7,22,28,30,32-pentahydroxy-6[(2R)-4-methyl-2-(methylamino) valeramido]-2,5,24,38,39-pentaoxo-22H-8,11:18,21-dietheno23, 36-(iminomethano)-13, 16:31, 35-dimetheno-1H, 16H-[l, 6, 9] oxadiazacyclohexadecino [4, 5-m] [10, 2, 16]-benzoxadiazacyclotetracosine-26-carboxylic acid, monohydrochloride. The molecular formula is C66H75Cl2N9O24·HCl and the molecular weight is 1,485.71. Vancomycin hydrochloride has the following structural formula:

Vancomycin Injection, USP in the GALAXY container is a frozen, iso-osmotic, sterile, nonpyrogenic, premixed single-dose formulation. The composition of Vancomycin Injection, USP, available in the following strengths are:

- 500 mg/100 mL (5 mg/mL): containing 500 mg of vancomycin (equivalent to 513 mg of vancomycin hydrochloride); approximately 5 g of dextrose hydrous or 0.9 g of sodium chloride (equivalent to 354 mg total sodium content)
- 750 mg/150 mL (5 mg/mL): containing 750 mg of vancomycin (equivalent to 769 mg of vancomycin hydrochloride); approximately 7.5 g of dextrose hydrous or 1.35 g of sodium chloride (equivalent to 531 mg total sodium content)
- 1 g/200 mL (5 mg/mL): containing 1 g of vancomycin (equivalent to 1.025 g of vancomycin hydrochloride); approximately 10 g of dextrose hydrous or 1.8 g of sodium chloride (equivalent to 708 mg total sodium content)
- 1.25 g/250 mL (5 mg/mL): containing 1.25 g of vancomycin (equivalent to 1.281 g of vancomycin hydrochloride); approximately 12.5 g of dextrose hydrous.
- 1.5 g/300 mL (5 mg/mL): containing 1.5 g of vancomycin (equivalent to 1.538 g of vancomycin hydrochloride); approximately 15 g of dextrose hydrous.

The pH of the solution may have been adjusted with hydrochloric acid and/or sodium hydroxide. Thawed solutions have a pH in the range of 3.0 to 5.0. After thawing to room temperature, this solution is intended for intravenous use only.

This GALAXY container is fabricated from a specially designed multilayer plastic. Solutions are in contact with the polyethylene layer of this container and can leach out certain chemical components of the plastic in very small amounts within the expiration period. The suitability of the plastic has been confirmed in tests in animals according to USP biological tests for plastic containers as well as by tissue culture toxicity studies.

12 CLINICAL PHARMACOLOGY

12.1 Mechanism of Action

Vancomycin is an antibacterial drug [see Microbiology (12.4)].

12.2 Pharmacodynamics

Based on animal models of infection, the antimicrobial activity of vancomycin appears to correlate with the AUC/MIC (area under the concentration-time curve/minimum inhibitory concentration) ratio for certain pathogens, including methicillin resistant Staphylococcus aureus. The principal pharmacokinetic/pharmacodynamic parameter best associated with clinical and microbiological cure has not been elucidated in clinical trials^2,3.

12.3 Pharmacokinetics

General Pharmacokinetics

In subjects with normal kidney function, multiple intravenous dosing of 1 g of vancomycin (15 mg/kg) infused over 60 minutes produces mean plasma concentrations of approximately 63 mcg/mL immediately after the completion of infusion, mean plasma concentrations of approximately 23 mcg/mL 2 hours after infusion, and mean plasma concentrations of approximately 8 mcg/mL 11 hours after the end of the infusion. Multiple dosing of 500 mg infused over 30 minutes produces mean plasma concentrations of about 49 mcg/mL at the completion of infusion, mean plasma concentrations of about 19 mcg/mL 2 hours after infusion, and mean plasma concentrations of about 10 mcg/mL 6 hours after infusion. The plasma concentrations during multiple dosing are similar to those after a single dose.

Distribution

The distribution coefficient is from 0.3 to 0.43 L/kg. Vancomycin is approximately 55% serum protein bound as measured by ultrafiltration at vancomycin serum concentrations of 10 to 100 mcg/mL. After IV administration of vancomycin, inhibitory concentrations are present in pleural, pericardial, ascitic, and synovial fluids; in urine; in peritoneal dialysis fluid; and in atrial appendage tissue. Vancomycin does not readily diffuse across normal meninges into the spinal fluid; but, when the meninges are inflamed, penetration into the spinal fluid occurs.

Elimination

Mean plasma clearance is about 0.058 L/kg/h, and mean renal clearance is about 0.048 L/kg/h. The mean elimination half-life of vancomycin from plasma is 4 to 6 hours in subjects with normal renal function. In anephric patients, the average half-life of elimination is 7.5 days. Total systemic and renal clearance of vancomycin may be reduced in the elderly.

Metabolism

There is no apparent metabolism of vancomycin.

Excretion

In the first 24 hours, about 75% of an administered dose of vancomycin is excreted in urine by glomerular filtration. Renal dysfunction slows excretion of vancomycin.

12.4 Microbiology

Mechanism of Action

The bactericidal action of vancomycin results primarily from inhibition of cell-wall biosynthesis. In addition, vancomycin alters bacterial-cell-membrane permeability and RNA synthesis.

Resistance

There is no cross-resistance between vancomycin and other antibacterial(s). Vancomycin is not active in vitro against gram-negative bacilli, mycobacteria, or fungi.

Interaction With Other Antimicrobials

The combination of vancomycin and an aminoglycoside acts synergistically in vitro against many isolates of Staphylococcus aureus, Streptococcus gallolyticus (previously known as Streptococcus bovis), Enterococcus spp, and the viridans group streptococci.

Antimicrobial Activity

Vancomycin has been shown to be active against most isolates of the following bacteria, both in vitro and in clinical infections [see Indications and Usage section (1)].

Aerobic bacteria

Gram-positive bacteria

Corynebacterium spp.
  Enterococcus spp. (including Enterococcus faecalis)
  Staphylococcus aureus (including methicillin-resistant and methicillin-susceptible isolates)
Coagulase negative staphylococci (including S. epidermidis and methicillin-resistant isolates)
Streptococcus gallolyticus (previously known as Streptococcus bovis)
Viridans group streptococci

The following in vitro data are available, but their clinical significance is unknown. At least 90 percent of the following bacteria exhibit an in vitro minimum inhibitory concentration (MIC) less than or equal to the susceptible breakpoint for vancomycin against isolates of similar genus or organism group. However, the efficacy of vancomycin in treating clinical infections caused by these bacteria has not been established in adequate and well-controlled clinical trials.

Aerobic bacteria

Gram-positive bacteria

Listeria monocytogenes
  Streptococcus pyogenes
  Streptococcus pneumoniae
  Streptococcus agalactiae

Anaerobic bacteria

Gram-positive bacteria

Actinomyces spp
  Lactobacillus spp

Susceptibility Testing

For specific information regarding susceptibility test interpretive criteria and associated test methods and quality control standards recognized by FDA for this drug, please see: https://www.fda.gov/STIC.

13 NONCLINICAL TOXICOLOGY

13.1 Carcinogenesis, Mutagenesis, Impairment of Fertility

No long-term studies in animals have been performed to evaluate carcinogenic potential. No definitive fertility studies have been performed.

13.2 Animal Toxicology and/or Pharmacology

In animal studies, hypotension and bradycardia occurred in dogs receiving an intravenous infusion of vancomycin 25 mg/kg, at a concentration of 25 mg/mL and an infusion rate of 13.3 mL/min.

15 REFERENCES

1. Byrd RA., Gries CL, Buening M.: Developmental Toxicology Studies of Vancomycin Hydrochloride Administered Intravenously to Rats and Rabbits. Fundam Appl Toxicol 1994; 23: 590-597.
2. Rybak MJ. The pharmacokinetic and pharmacodynamic properties of vancomycin. Clinical Infectious Diseases. 2006;42(Supplement_1): S35-S39.
3. Rybak MJ, Le J, Lodise TP, et al. Therapeutic monitoring of vancomycin for serious methicillin-resistant Staphylococcus aureus infections: a revised consensus guideline and review by the American Society of Health-System Pharmacists, the Infectious Diseases Society of America, the Pediatric Infectious Diseases Society, and the Society of Infectious Diseases Pharmacists. Clinical Infectious Diseases. 2020;71(6):1361-1364.

16 HOW SUPPLIED/STORAGE AND HANDLING

How Supplied

Vancomycin Injection, USP is supplied as a frozen, iso-osmotic, premixed solution packaged in a single-dose GALAXY plastic container and is available as follows:

Supply Information for Vancomycin Injection, in 5% Dextrose
Strength | Number of Containers/ Carton | NDC
500 mg of vancomycin / 100 mL (5 mg/mL) | 12 count | 0338-3551-48
750 mg of vancomycin / 150 mL (5 mg/mL) | 6 count | 0338-3580-48
1 g of vancomycin / 200 mL (5mg/mL) | 6 count | 0338-3552-48
1.25 g of vancomycin / 250 mL (5 mg/mL) | 4 count | 0338-0122-04
1.5 g of vancomycin / 300 mL (5 mg/mL) | 4 count | 0338-0124-04

Supply Information for Vancomycin Injection, in 0.9% Sodium Chloride
Strength | Number of Containers/ Carton | NDC
500 mg of vancomycin / 100 mL (5 mg/mL) | 12 count | 0338-3581-01
750 mg vancomycin / 150 mL (5 mg/mL) | 6 count | 0338-3582-01
1 g of vancomycin / 200 mL (5mg/mL) | 6 count | 0338-3583-01

Storage

Store Vancomycin Injection at or below -20°C (-4°F) or Store in a freezer capable of maintaining a temperature at or below -20°C (-4°F). Storage of the thawed solution is described elsewhere in the labeling [see Dosage and Administration (2.5)]

Handling

Handle frozen product containers with care. Product containers may be fragile in the frozen state.

17 PATIENT COUNSELING INFORMATION

Infusion Reactions During or After Intravenous Use

Advise patients that generalized skin redness, skin rash, itching, flushing, muscle pain, chest pain, shortness of breath, wheezing, or dizziness may occur during intravenous infusion of Vancomycin Injection. [see Warnings and Precautions (5.1)].

Acute Kidney Injury

Advise patients that Vancomycin Injection can result in kidney damage and that blood tests are required to monitor vancomycin blood levels and kidney function during therapy [see Warnings and Precautions (5.2)].

Hearing Loss or Balance Problems

Advise patients that Vancomycin injection may result in decreased hearing and to report hearing loss or balance problems to their healthcare provider [see Warnings and Precautions (5.3)].

Severe Dermatologic Reactions

Advise patients about the signs and symptoms of serious skin manifestations. Instruct patients to stop Vancomycin Injection immediately and promptly seek medical attention at the first signs or symptoms of skin rash, mucosal lesions and blisters [see Warnings and Precautions (5.4)].

Diarrhea

Diarrhea is a common problem caused by antibacterial drugs, including Vancomycin Injection, which usually ends when the antibacterial drug is discontinued. Sometimes after starting treatment with antibacterial drugs, patients can develop watery and bloody stools (with or without stomach cramps and fever) even as late as two or more months after having taken the last dose of the antibacterial drug. If this occurs, patients should contact their physician as soon as possible [see Warnings and Precautions (5.5)].

Antibacterial Resistance

Patients should be counseled that antibacterial drugs including Vancomycin Injection, should only be used to treat bacterial infections. They do not treat viral infections (e.g., the common cold). When Vancomycin Injection is prescribed to treat a bacterial infection, patients should be told that although it is common to feel better early in the course of therapy, the medication should be taken exactly as directed. Skipping doses or not completing the full course of therapy may (1) decrease the effectiveness of the immediate treatment and (2) increase the likelihood that bacteria will develop resistance and will not be treatable by Vancomycin Injection or other antibacterial drugs in the future.

Manufactured by, Packed by, Distributed by:

Baxter Healthcare Corporation
Deerfield, IL 60015 USA
Made in the USA

07-19-08-903

Baxter and Galaxy are trademarks of Baxter International Inc. or its subsidiaries.

PACKAGE/LABEL PRINCIPAL DISPLAY PANEL

Container Label

NDC 0338-3551-48

Vancomycin Injection, USP
in 5% Dextrose

500 mg per 100 mL
(5 mg/mL)

GALAXY
Single-Dose Container
Discard unused portion

Code 2G3551
Sterile Nonpyrogenic
Iso-osmotic

Each 100 mL contains: Vancomycin Hydrochloride, USP equivalent to
500 mg vancomycin with approx. 5 g Dextrose Hydrous, USP in Water for
Injection, USP. pH may have been adjusted with hydrochloric acid and/or
sodium hydroxide.

Dosage: For intravenous use only. See prescribing information.

Cautions: Do not add supplementary medication or additives.

Rx Only
Store at or below -20°C (-4°F). Thaw at room temperature
(25°C/77°F) or under refrigeration (5°C/41°F). Product should not
be thawed by immersion in water baths or by microwave irradiation.
Do not force thaw. Thawed solution is stable for 30 days under
refrigeration or 72 hours at room temperature. Do not refreeze.

PL 2040 Plastic

Baxter Logo

Baxter and Galaxy are trademarks of
Baxter International Inc.
Baxter Healthcare Corporation, Deerfield, IL 60015 USA

07-34-74-761

Carton Label

Thaw at room temperature (25°C/77°F) or under refrigeration (5°C/41°F). Product should not be thawed by immersion in water baths or by microware irradiation. Do not force thaw. The thawed solution in GALAXY plastic container (PL 2040) remains chemically stable for 72 hours at room temperature or for 30 days when stored under refrigeration. Do not refreeze.

Handle frozen product containers with care. Product containers may be fragile in the frozen state.

PL 2040 Plastic 07-04-74-764

Vancomycin Injection, USP in 5% Dextrose
500 mg per 100 mL (5 mg/ mL)
Contains 6 Single-Use bags. Each bag contains 100 mL. Iso-osmotic. Store at or below -20°C/-4°F.

Rx Only

NDC 0338-3551-48
Code 2G3551

*FOR BAR CODE POSITION ONLY
(01) 20303383551485

GALAXY Container

Sterile Nonpyrogenic

Each 100 mL contains: Vancomycin Hydrochloride, USP equivalent to 500 mg vancomycin with approx. 5 g Dextrose Hydrous, USP in Water for Injection, USP. pH may have been adjusted with hydrochloric acid and/or sodium hydroxide.

Dosage: For intravenous use only. See prescribing information.
Cautions: Do not add supplementary medication or additives.

Baxter Logo

Baxter and Galaxy are registered trademarks of Baxter International Inc.
Baxter Healthcare Corporation, Deerfield, IL 60015 USA

Container Label

NDC 0338-3552-48

Vancomycin Injection, USP
in 5% Dextrose

1 g per 200 mL
(5 mg/mL)

GALAXY
Single-Dose Container
Discard unused portion

Code 2G3552
Sterile Nonpyrogenic
Iso-osmotic

Each 100 mL contains: Vancomycin Hydrochloride, USP
equivalent to 500 mg vancomycin with approx. 5 g Dextrose
Hydrous, USP in Water for Injection, USP. pH may have been
adjusted with hydrochloric acid and/or sodium hydroxide.

Dosage: For intravenous use only. See prescribing information.

Cautions: Do not add supplementary medication or additives.

Rx Only
Store at or below -20°C (-4°F). Thaw at room temperature
(25°C/77°F) or under refrigeration (5°C/41°F). Product should
not be thawed by immersion in water baths or by microwave
irradiation. Do not force thaw. Thawed solution is stable for 30
days under refrigeration or 72 hours at room temperature.
Do not refreeze.

PL 2040 Plastic

Baxter Logo

Baxter and Galaxy are trademarks of
Baxter International Inc.
Baxter Healthcare Corporation, Deerfield, IL 60015 USA

07-34-74-763

Carton Labels

Thaw at room temperature (25°C/77°F) or under refrigeration (5°C/41°F). Product should not be thawed by immersion in water baths or by microware irradiation. Do not force thaw. The thawed solution in GALAXY plastic container (PL 2040) remains chemically stable for 72 hours at room temperature or for 30 days when stored under refrigeration. Do not refreeze.

Handle frozen product containers with care. Product containers may be fragile in the frozen state.

PL 2040 Plastic 07-04-74-766

Vancomycin Injection, USP in 5% Dextrose
1 g per 200 mL (5 mg/ mL)
Contains 3 Single-Use bags. Each bag contains 200 mL. Iso-osmotic. Store at or below -20°C/-4°F.

Rx Only

NDC 0338-3552-48
Code 2G3552

*FOR BAR CODE POSITION ONLY
(01) 20303383552482

GALAXY Container

Sterile Nonpyrogenic

Each 100 mL contains: Vancomycin Hydrochloride, USP equivalent to 500 mg vancomycin with approx. 5 g Dextrose Hydrous, USP in Water for Injection, USP. pH may have been adjusted with hydrochloric acid and/or sodium hydroxide.

Dosage: For intravenous use only. See prescribing information.
Cautions: Do not add supplementary medication or additives.

Baxter Logo

Baxter and Galaxy are registered trademarks of Baxter International Inc.
Baxter Healthcare Corporation, Deerfield, IL 60015 USA

Container Label

NDC 0338-3580-48

Vancomycin Injection, USP
in 5% Dextrose

750 mg per 150 mL
(5 mg/mL)

GALAXY
Single-Dose Container
Discard unused portion

Code 2G3580
Sterile Nonpyrogenic
Iso-osmotic

Each 100 mL contains: Vancomycin Hydrochloride, USP
equivalent to 500 mg vancomycin with approx. 5 g Dextrose
Hydrous, USP in Water for Injection, USP. pH may have been
adjusted with hydrochloric acid and/or sodium hydroxide.

Dosage: For intravenous use only. See prescribing information.

Cautions: Do not add supplementary medication or additives.

Rx Only
Store at or below -20°C (-4°F). Thaw at room temperature
(25°C/77°F) or under refrigeration (5°C/41°F). Product should
not be thawed by immersion in water baths or by microwave
irradiation. Do not force thaw. Thawed solution is stable for 30
days under refrigeration or 72 hours at room temperature.
Do not refreeze.

PL 2040 Plastic

Baxter Logo

Baxter and Galaxy are trademarks of
Baxter International Inc.
Baxter Healthcare Corporation, Deerfield, IL 60015 USA

07-34-74-762

Carton Labels

Thaw at room temperature (25°C/77°F) or under refrigeration (5°C/41°F). Product should not be thawed by immersion in water baths or by microware irradiation. Do not force thaw. The thawed solution in GALAXY plastic container (PL 2040) remains chemically stable for 72 hours at room temperature or for 30 days when stored under refrigeration. Do not refreeze.

Handle frozen product containers with care. Product containers may be fragile in the frozen state.

PL 2040 Plastic 07-04-74-765

Vancomycin Injection, USP in 5% Dextrose
750 mg per 150 mL (5 mg/ mL)
Contains 3 Single-Use bags. Each bag contains 150 mL. Iso-osmotic. Store at or below -20°C/-4°F.

Rx Only

NDC 0338-3580-48
Code 2G3580

*FOR BAR CODE POSITION ONLY
(01) 20303383580485

GALAXY Container

Sterile Nonpyrogenic

Each 100 mL contains: Vancomycin Hydrochloride, USP equivalent to 500 mg vancomycin with approx. 5 g Dextrose Hydrous, USP in Water for Injection, USP. pH may have been adjusted with hydrochloric acid and/or sodium hydroxide.

Dosage: For intravenous use only. See prescribing information.
Cautions: Do not add supplementary medication or additives.

Baxter Logo

Baxter and Galaxy are registered trademarks of Baxter International Inc.
Baxter Healthcare Corporation, Deerfield, IL 60015 USA

Container Label

NDC 0338-3581-01

Vancomycin Injection, USP
in 0.9% Sodium Chloride

500 mg per 100 mL
(5 mg/mL)

GALAXY
Single-Dose Container
Discard unused portion

Code 2G3590
Sterile Nonpyrogenic
Iso-osmotic

Each 100 mL contains: Vancomycin Hydrochloride, USP equivalent to
500 mg vancomycin with approx. 0.9 g Sodium Chloride, USP in Water for
Injection, USP. pH may have been adjusted with hydrochloric acid and/or
sodium hydroxide.

Dosage: For intravenous use only. See prescribing information.

Cautions: Do not add supplementary medication or additives.

Rx Only
Store at or below -20°C (-4°F). Thaw at room temperature
(25°C/77°F) or under refrigeration (5°C/41°F). Product should not
be thawed by immersion in water baths or by microwave irradiation.
Do not force thaw. Thawed solution is stable for 30 days under
refrigeration or 72 hours at room temperature. Do not refreeze.

PL 2040 Plastic

Baxter Logo

Baxter and Galaxy are trademarks of
Baxter International Inc.
Baxter Healthcare Corporation, Deerfield, IL 60015 USA

07-34-74-548

Carton Labels

Thaw at room temperature (25°C/77°F) or under refrigeration (5°C/41°F). Product should not be thawed by immersion in water baths or by microware irradiation. Do not force thaw. The thawed solution in GALAXY plastic container (PL 2040) remains chemically stable for 72 hours at room temperature or for 30 days when stored under refrigeration. Do not refreeze.

Handle frozen product containers with care. Product containers may be fragile in the frozen state.

PL 2040 Plastic 07-04-77-715

Vancomycin Injection, USP in 0.9% Sodium Chloride
500 mg per 100 mL (5 mg/ mL)
Contains 6 Single-Dose bags. Each bag contains 100 mL. Iso-osmotic. Store at or below -20°C/-4°F.

Rx Only

NDC 0338-3581-01
Code 2G3590

*FOR BAR CODE POSITION ONLY
(01) 20303383581017

GALAXY Container

Sterile Nonpyrogenic

Each 100 mL contains: Vancomycin Hydrochloride, USP equivalent to 500 mg vancomycin with approx. 0.9 Sodium Chloride, USP in Water for Injection, USP. pH may have been adjusted with hydrochloric acid and/or sodium hydroxide.

Dosage: For intravenous use only. See prescribing information.
Cautions: Do not add supplementary medication or additives.

Baxter Logo

Baxter and Galaxy are registered trademarks of Baxter International Inc.
Baxter Healthcare Corporation, Deerfield, IL 60015 USA

Container Label

NDC 0338-3582-01

Vancomycin Injection, USP
in 0.9% Sodium Chloride

750 mg per 150 mL
(5 mg/mL)

GALAXY
Single-Dose Container
Discard unused portion

Code 2G3591
Sterile Nonpyrogenic
Iso-osmotic

Each 100 mL contains: Vancomycin Hydrochloride, USP
equivalent to 500 mg vancomycin with approx. 0.9 g Sodium
Chloride, USP in Water for Injection, USP. pH may have been
adjusted with hydrochloric acid and/or sodium hydroxide.

Dosage: For intravenous use only. See prescribing information.

Cautions: Do not add supplementary medication or additives.

Rx Only
Store at or below -20°C (-4°F). Thaw at room temperature
(25°C/77°F) or under refrigeration (5°C/41°F). Product should
not be thawed by immersion in water baths or by microwave
irradiation. Do not force thaw. Thawed solution is stable for 30
days under refrigeration or 72 hours at room temperature.
Do not refreeze.

PL 2040 Plastic

Baxter Logo

Baxter and Galaxy are trademarks of
Baxter International Inc.
Baxter Healthcare Corporation, Deerfield, IL 60015 USA

07-34-74-551

Carton Labels

Thaw at room temperature (25°C/77°F) or under refrigeration (5°C/41°F). Product should not be thawed by immersion in water baths or by microware irradiation. Do not force thaw. The thawed solution in GALAXY plastic container (PL 2040) remains chemically stable for 72 hours at room temperature or for 30 days when stored under refrigeration. Do not refreeze.

Handle frozen product containers with care. Product containers may be fragile in the frozen state.

PL 2040 Plastic 07-04-77-715

Vancomycin Injection, USP in 0.9 Sodium Chloride
750 mg per 150 mL (5 mg/ mL)
Contains 3 Single-Dose bags. Each bag contains 150 mL. Iso-osmotic. Store at or below -20°C/-4°F.

Rx Only

NDC 0338-3582-01
Code 2G3591

*FOR BAR CODE POSITION ONLY
(01) 20303383582014

GALAXY Container

Sterile Nonpyrogenic

Each 100 mL contains: Vancomycin Hydrochloride, USP equivalent to 500 mg vancomycin with approx. 0.9 Sodium Chloride, USP in Water for Injection, USP. pH may have been adjusted with hydrochloric acid and/or sodium hydroxide.

Dosage: For intravenous use only. See prescribing information.
Cautions: Do not add supplementary medication or additives.

Baxter Logo

Baxter and Galaxy are registered trademarks of Baxter International Inc.
Baxter Healthcare Corporation, Deerfield, IL 60015 USA

Container Label

NDC 0338-3583-01

Vancomycin Injection, USP
in 0.9% Sodium Chloride

1 g per 200 mL
(5 mg/mL)

GALAXY
Single-Dose Container
Discard unused portion

Code 2G3592
Sterile Nonpyrogenic
Iso-osmotic

Each 100 mL contains: Vancomycin Hydrochloride, USP
equivalent to 500 mg vancomycin with approx. 0.9 g Sodium
Chloride, USP in Water for Injection, USP. pH may have been
adjusted with hydrochloric acid and/or sodium hydroxide.

Dosage: For intravenous use only. See prescribing information.

Cautions: Do not add supplementary medication or additives.

Rx Only
Store at or below -20°C (-4°F). Thaw at room temperature
(25°C/77°F) or under refrigeration (5°C/41°F). Product should
not be thawed by immersion in water baths or by microwave
irradiation. Do not force thaw. Thawed solution is stable for 30
days under refrigeration or 72 hours at room temperature.
Do not refreeze.

PL 2040 Plastic

Baxter Logo

Baxter and Galaxy are trademarks of
Baxter International Inc.
Baxter Healthcare Corporation, Deerfield, IL 60015 USA

07-34-74-553

Carton Labels

Thaw at room temperature (25°C/77°F) or under refrigeration (5°C/41°F). Product should not be thawed by immersion in water baths or by microware irradiation. Do not force thaw. The thawed solution in GALAXY plastic container (PL 2040) remains chemically stable for 72 hours at room temperature or for 30 days when stored under refrigeration. Do not refreeze.

Handle frozen product containers with care. Product containers may be fragile in the frozen state.

PL 2040 Plastic 07-04-77-717

Vancomycin Injection, USP in 0.9 Sodium Chloride
1 g per 200 mL (5 mg/ mL)
Contains 3 Single-Dose bags. Each bag contains 200 mL. Iso-osmotic. Store at or below -20°C/-4°F.

Rx Only

NDC 0338-3583-01
Code 2G3592

*FOR BAR CODE POSITION ONLY
(01) 20303383583011

GALAXY Container

Sterile Nonpyrogenic

Each 100 mL contains: Vancomycin Hydrochloride, USP equivalent to 500 mg vancomycin with approx. 0.9 Sodium Chloride, USP in Water for Injection, USP. pH may have been adjusted with hydrochloric acid and/or sodium hydroxide.

Dosage: For intravenous use only. See prescribing information.
Cautions: Do not add supplementary medication or additives.

Baxter Logo

Baxter and Galaxy are registered trademarks of Baxter International Inc.
Baxter Healthcare Corporation, Deerfield, IL 60015 USA

Container Label

NDC 0338-0122-04

1.25 g

Vancomycin Injection, USP
in 5% Dextrose

1.25 g per 250 mL (5 mg/mL)

For Intravenous Infusion Only
Single-Dose GALAXY Container
Discard Unused Portion

Rx Only
Sterile

Each 100 mL contains: Vancomycin Hydrochloride, USP equivalent to 500 mg
vancomycin with approx. 5 g Dextrose Hydrous, USP in Water for Injection, USP.
Dosage: See prescribing information.

Store frozen at or below -20°C /-4°F.

Thaw at room temperature 20°C to 25°C (68°F to 77°F) or under refrigeration 2°C to 8°C (36°F to 46°F)
and store thawed solution as follows:
– Refrigerated Storage: Use within 30 days
– Room Temperature Storage: Use within 72 hours
Do not force thaw. Do not refreeze the thawed solution.
Do not add supplemental medication or additives.

Code 2G3557

Baxter Logo

Baxter and Galaxy are trademarks of Baxter International Inc. or its subsidiaries.
Baxter Healthcare Corporation, Deerfield, IL 60015 USA

07-34-00-1841

*UPC-A BAR CODE
POSITION ONLY

309440495057

Carton Label

Store frozen at or below -20°C /-4°F. Thaw at room temperature 20°C to 25°C (68°F to 77°F) or under refrigeration
2°C to 8°C (36°F to 46°F) and store thawed solution as follows:
– Refrigerated Storage: Use within 30 days
– Room Temperature Storage: Use within 72 hours
Do not force thaw. Do not refreeze the thawed solution
Handle frozen product containers with care. Product containers may be fragile in the frozen state.

07-04-00-0961

1.25 g

Vancomycin Injection, USP
in 5% Dextrose

1.25 g per 250 mL (5 mg/mL)

For Intravenous Infusion Only.

Contains 2 units of Single-Dose bags.
Each bag contains 250 mL.
Store at or below -20°C/-4°F.

Rx Only

NDC 0338-0122-04
Code 2G3557

*FOR BAR CODE POSITION ONLY
(01)00000000000000

GALAXY Container
Sterile

Each 100 mL contains: Vancomycin Hydrochloride, USP equivalent to 500 mg vancomycin with approx.
5 g Dextrose Hydrous, USP in Water for Injection, USP.

Dosage: See prescribing information.
Do not add supplementary medication or additives.

Baxter Logo

Baxter and Galaxy are trademarks of Baxter International Inc. or its subsidiaries.
Baxter Healthcare Corporation, Deerfield, IL 60015 USA

Container Label

NDC 0338-0124-04

1.5 g

Vancomycin Injection, USP
in 5% Dextrose

1.5 g per 300 mL (5 mg/mL)

For Intravenous Infusion Only
Single-Dose GALAXY Container
Discard Unused Portion

Rx Only
Sterile

Each 100 mL contains: Vancomycin Hydrochloride, USP equivalent to 500 mg
vancomycin with approx. 5 g Dextrose Hydrous, USP in Water for Injection, USP.
Dosage: See prescribing information.

Store frozen at or below -20°C /-4°F.

Thaw at room temperature 20°C to 25°C (68°F to 77°F) or under refrigeration 2°C to 8°C (36°F to 46°F)
and store thawed solution as follows:
– Refrigerated Storage: Use within 30 days
– Room Temperature Storage: Use within 72 hours
Do not force thaw. Do not refreeze the thawed solution.
Do not add supplemental medication or additives.

Code 2G3558

Baxter Logo

Baxter and Galaxy are trademarks of Baxter International Inc. or its subsidiaries.
Baxter Healthcare Corporation, Deerfield, IL 60015 USA

07-34-00-1842

*UPC-A BAR CODE
POSITION ONLY

309440495057

Carton Label

Store frozen at or below -20°C /-4°F. Thaw at room temperature 20°C to 25°C (68°F to 77°F) or under refrigeration
2°C to 8°C (36°F to 46°F) and store thawed solution as follows:
– Refrigerated Storage: Use within 30 days
– Room Temperature Storage: Use within 72 hours
Do not force thaw. Do not refreeze the thawed solution
Handle frozen product containers with care. Product containers may be fragile in the frozen state.

07-04-00-0962

1.5 g

Vancomycin Injection, USP
in 5% Dextrose

1.5 g per 300 mL (5 mg/mL)

For Intravenous Infusion Only.

Contains 2 units of Single-Dose bags.
Each bag contains 300 mL.
Store at or below -20°C/-4°F.

Rx Only

NDC 0338-0124-04
Code 2G3558

*FOR BAR CODE POSITION ONLY
(01)00000000000000

GALAXY Container
Sterile

Each 100 mL contains: Vancomycin Hydrochloride, USP equivalent to 500 mg vancomycin with approx.
5 g Dextrose Hydrous, USP in Water for Injection, USP.
Dosage: See prescribing information.
Do not add supplementary medication or additives.

Baxter Logo

Baxter and Galaxy are trademarks of Baxter International Inc. or its subsidiaries.
Baxter Healthcare Corporation, Deerfield, IL 60015 USA